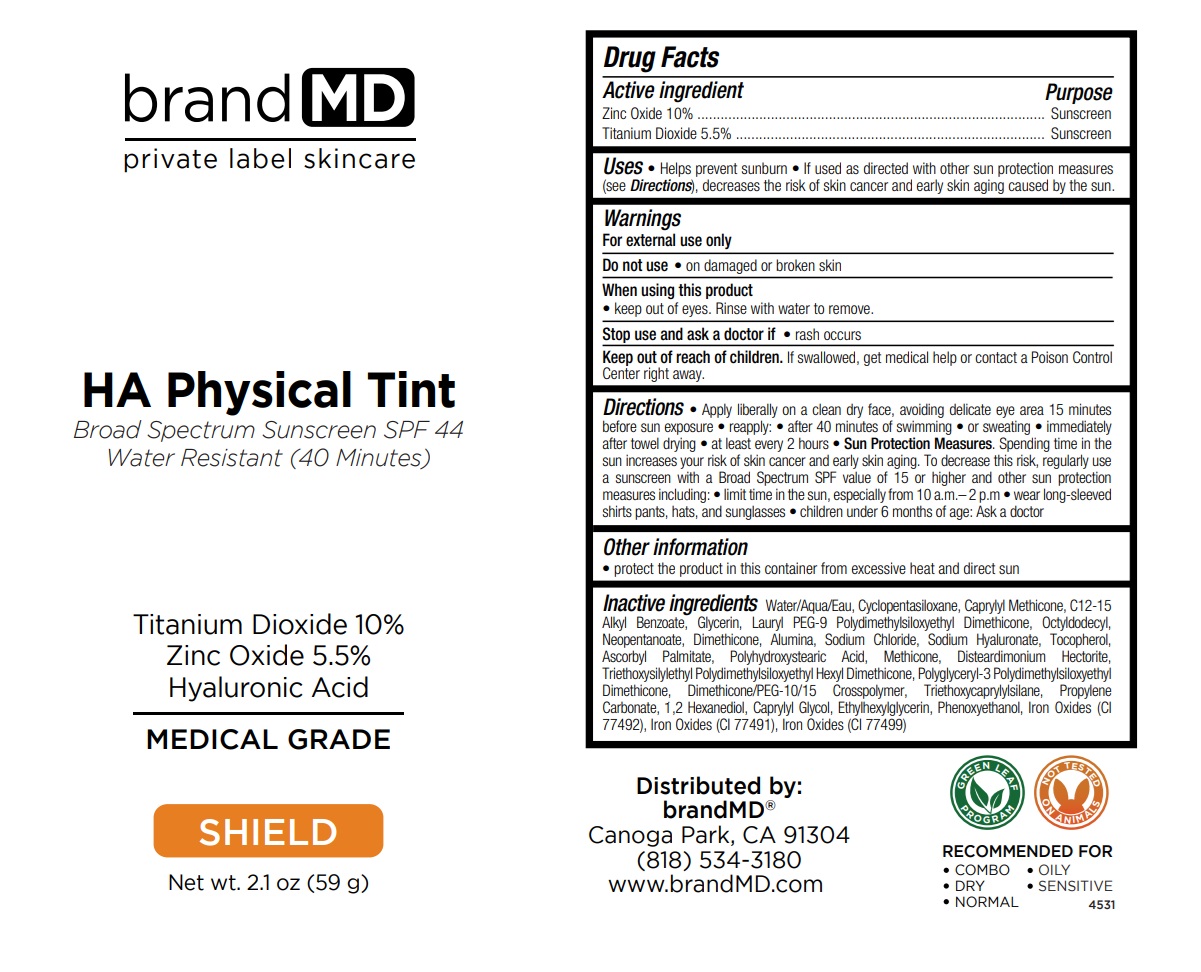 DRUG LABEL: HA Physical Tint SPF 44
NDC: 72957-006 | Form: CREAM
Manufacturer: Private Label Skin Care
Category: otc | Type: HUMAN OTC DRUG LABEL
Date: 20250227

ACTIVE INGREDIENTS: ZINC OXIDE 10 g/100 g; TITANIUM DIOXIDE 5.5 g/100 g
INACTIVE INGREDIENTS: WATER; CYCLOMETHICONE 5; CAPRYLYL TRISILOXANE; ALKYL (C12-15) BENZOATE; GLYCERIN; LAURYL PEG-9 POLYDIMETHYLSILOXYETHYL DIMETHICONE; OCTYLDODECYL NEOPENTANOATE; DIMETHICONE, UNSPECIFIED; ALUMINUM OXIDE; SODIUM CHLORIDE; HYALURONATE SODIUM; TOCOPHEROL; ASCORBYL PALMITATE; POLYHYDROXYSTEARIC ACID (2300 MW); METHICONE (20 CST); DISTEARDIMONIUM HECTORITE; TRIETHOXYSILYLETHYL POLYDIMETHYLSILOXYETHYL HEXYL DIMETHICONE; POLYGLYCERYL-3 POLYDIMETHYLSILOXYETHYL DIMETHICONE (4000 MPA.S); DIMETHICONE/PEG-10/15 CROSSPOLYMER; TRIETHOXYCAPRYLYLSILANE; PROPYLENE CARBONATE; 1,2-HEXANEDIOL; CAPRYLYL GLYCOL; ETHYLHEXYLGLYCERIN; PHENOXYETHANOL; FERRIC OXIDE YELLOW; FERRIC OXIDE RED; FERROSOFERRIC OXIDE

HA Physical Tint SPF 44

Active ingredient

Zinc Oxide 10%

Titanium Dioxide 5.5%

Purpose

Sunscreen

Uses

• Helps prevent sunburn • If used as directed with other sun protection measures (see Directions), decreases the risk of skin cancer and early skin aging caused by the sun.

Warnings

For external use only

Do not use • on damaged or broken skin

When using this product
• keep out of eyes. Rinse with water to remove.

Stop use and ask a doctor if • rash occurs

Keep out of reach of children. If swallowed, get medical help or contact a Poison Control Center right away.

Directions

• Apply liberally on a clean dry face, avoiding delicate eye area 15 minutes before sun exposure • reapply: • after 40 minutes of swimming • or sweating • immediately after towel drying • at least every 2 hours • Sun Protection Measures. Spending time in the sun increases your risk of skin cancer and early skin aging. To decrease this risk, regularly use a sunscreen with a Broad Spectrum SPF value of 15 or higher and other sun protection measures including: • limit time in the sun, especially from 10 a.m.– 2 p.m • wear long-sleeved shirts pants, hats, and sunglasses • children under 6 months of age: Ask a doctor

Other information

• protect the product in this container from excessive heat and direct sun

Inactive ingredients

Water/Aqua/Eau, Cyclopentasiloxane, Caprylyl Methicone, C12-15 Alkyl Benzoate, Glycerin, Lauryl PEG-9 Polydimethylsiloxyethyl Dimethicone, Octyldodecyl Neopentanoate, Dimethicone, Alumina, Sodium Chloride, Sodium Hyaluronate, Tocopherol, Ascorbyl Palmitate, Polyhydroxystearic Acid, Methicone, Disteardimonium Hectorite, Triethoxysilylethyl Polydimethylsiloxyethyl Hexyl Dimethicone, Polyglyceryl-3 Polydimethylsiloxyethyl Dimethicone, Dimethicone/PEG-10/15 Crosspolymer, Triethoxycaprylylsilane, Propylene Carbonate, 1,2 Hexanediol, Caprylyl Glycol, Ethylhexylglycerin, Phenoxyethanol, Iron Oxides (CI 77492), Iron Oxides (CI 77491), Iron Oxides (CI 77499)

brand MD

Broad Spectrum Sunscreen
Water Resistant (40 Minutes)

Titanium Dioxide 10%
Zinc Oxide 5.5%
Hyaluronic Acid

MEDICAL GRADE

SHIELD

RECOMMENDED FOR
• COMBO • OILY
• DRY • SENSITIVE
• NORMAL

GREEN LEAF PROGRAM

NOT TESTED ON ANIMALS

Distributed by:
brandMD®
Canoga Park, CA 91304
(818) 534-3180
www.brandMD.com